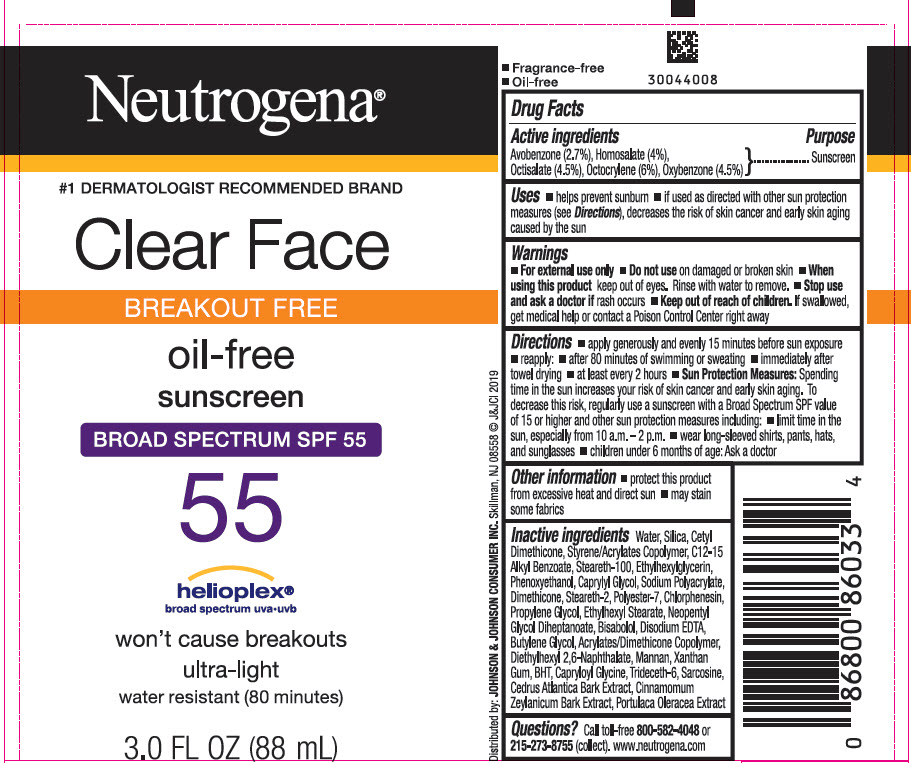 DRUG LABEL: Neutrogena Clear Face Breakout Free Oil Free Broad Spectrum SPF 55
NDC: 69968-0573 | Form: LOTION
Manufacturer: Kenvue Brands LLC
Category: otc | Type: HUMAN OTC DRUG LABEL
Date: 20251106

ACTIVE INGREDIENTS: AVOBENZONE 27 mg/1 mL; HOMOSALATE 40 mg/1 mL; OCTISALATE 45 mg/1 mL; OCTOCRYLENE 60 mg/1 mL; OXYBENZONE 45 mg/1 mL
INACTIVE INGREDIENTS: WATER; SILICON DIOXIDE; CETYL DIMETHICONE 25; ALKYL (C12-15) BENZOATE; STEARETH-100; ETHYLHEXYLGLYCERIN; PHENOXYETHANOL; CAPRYLYL GLYCOL; DIMETHICONE; STEARETH-2; POLYESTER-7; CHLORPHENESIN; PROPYLENE GLYCOL; ETHYLHEXYL STEARATE; NEOPENTYL GLYCOL DIHEPTANOATE; LEVOMENOL; EDETATE DISODIUM ANHYDROUS; BUTYLENE GLYCOL; BUTYL METHACRYLATE/METHYL METHACRYLATE/METHACRYLIC ACID/STYRENE CROSSPOLYMER; DIETHYLHEXYL 2,6-NAPHTHALATE; YEAST MANNAN; XANTHAN GUM; BUTYLATED HYDROXYTOLUENE; CAPRYLOYL GLYCINE; TRIDECETH-6; SARCOSINE; CEDRUS ATLANTICA BARK; CINNAMON BARK OIL; PURSLANE

Neutrogena® clear face BREAK-OUT FREE liquid-lotion SUNSCREEN Broad Spectrum SPF 55

Drug Facts

ACTIVE INGREDIENT

Active Ingredients | Purpose
Avobenzone 2.7% | Sunscreen
Homosalate 4% | Sunscreen
Octisalate 4.5% | Sunscreen
Octocrylene 6% | Sunscreen
Oxybenzone 4.5% | Sunscreen

Uses

- helps prevent sunburn
- if used as directed with other sun protection measures (see Directions), decreases the risk of skin cancer and early skin aging caused by the sun

Warnings

- For external use only

- Do not use on damaged or broken skin

- When using this product keep out of eyes. Rinse with water to remove

- Stop use and ask a doctor if rash occurs

- Keep out of reach of children. If swallowed, get medical help or contact a Poison Control Center right away.

Directions

- apply generously 15 minutes before sun exposure
- reapply:
  - after 80 minutes of swimming or sweating
  - immediately after towel drying
  - at least every 2 hours
- Sun Protection Measures. Spending time in the sun increases your risk of skin cancer and early skin aging. To decrease this risk, regularly use a sunscreen with a Broad Spectrum SPF value of 15 or higher and other sun protection measures including:
  - limit time in the sun, especially from 10 a.m. - 2 p.m.
  - wear long-sleeved shirts, pants, hats, and sunglasses
- children under 6 months of age: Ask a doctor

Other Information

- protect this product from excessive heat and direct sun
- may stain some fabrics

Inactive Ingredients

Water, Silica, Cetyl Dimethicone, Styrene/Acrylates Copolymer, C12-15 Alkyl Benzoate, Steareth-100, Ethylhexylglycerin, Phenoxyethanol, Caprylyl Glycol, Sodium Polyacrylate, Dimethicone, Steareth-2, Polyester-7, Chlorphenesin, Propylene Glycol, Ethylhexyl Stearate, Neopentyl Glycol Diheptanoate, Bisabolol, Disodium EDTA, Butylene Glycol, Acrylates/Dimethicone Copolymer, Diethylhexyl 2,6-Naphthalate, Mannan, Xanthan Gum, BHT, Capryloyl Glycine, Trideceth-6, Sarcosine, Cedrus Atlantica Bark Extract, Cinnamomum Zeylanicum Bark Extract, Portulaca Oleracea Extract

Questions?

Call toll-free 800-582-4048 or 215-273-8755 (collect). www.neutrogena.com

Distributed by: JOHNSON & JOHNSON CONSUMER INC. Skillman, NJ 08558

PRINCIPAL DISPLAY PANEL - 88 mL Tube Label

Neutrogena®
#1 DERMATOLOGIST RECOMMENDED BRAND

Clear Face
BREAKOUT FREE
oil-free
sunscreen
BROAD SPECTRUM SPF 55

55

helioplex®
broad spectrum uva•uvb

won't cause breakouts
ultra-light

water resistant (80 minutes)

3.0 FL OZ (88 mL)